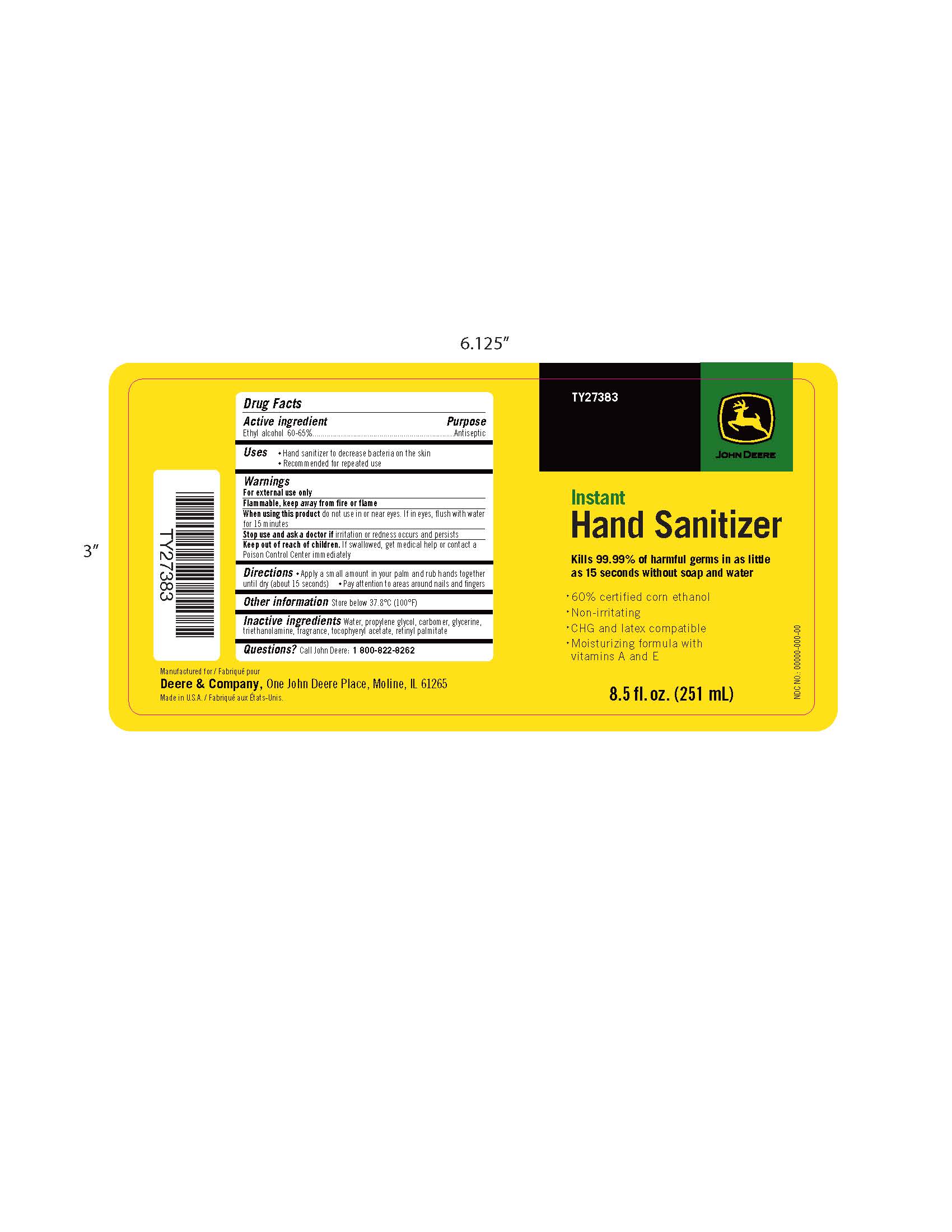 DRUG LABEL: John Deere Instant Hand Sanitizer
NDC: 70190-100 | Form: GEL
Manufacturer: TIG Distributing, Inc.
Category: otc | Type: HUMAN OTC DRUG LABEL
Date: 20181219

ACTIVE INGREDIENTS: ALCOHOL 600 mL/1000 mL
INACTIVE INGREDIENTS: WATER; PROPYLENE GLYCOL; CARBOMER HOMOPOLYMER TYPE C (ALLYL PENTAERYTHRITOL CROSSLINKED); GLYCERIN; TROLAMINE; .ALPHA.-TOCOPHEROL ACETATE; VITAMIN A PALMITATE

Drug Facts

Active Ingredients

Ethyl alcohol 60 - 65 %

Purpose

Antiseptic

Uses

- Hand sanitizer to decrease bacteria on the skin
- Recommended for repeated use

Warnings

For external use only

Flammable, keep away from fire or flame

When using this product do not use in or near eyes. If in eyes, flush with water

for 15 minutes.

Stop use and ask a doctor if irritation or redness occurs and persists.

Keep out of reach of children. If swallowed, get medical help or contact a

Poison Control Center immediately.

DOSAGE AND ADMINISTRATION

Directions - Apply a small amount in your palm and rub hands together

until dry (about 15 seconds) -Pay attention to areas around nails and fingers

Other information Store below 37.8 C (100 F)

Inactive ingredients Water, propylene glycol, carbomer, glycerine,

triethanolamine, fragrance, tocopheryl acetate, retinyl palmitate

Questions? Call John Deere: 1 800-822-8262

DESCRIPTION

Kills 99.99% of harmful germs in as little

as 15 seconds without soap and water

- 60% certified corn ethanol
- Non-irritating
- CHG and latex compatible
- Moisturizing formula with vitamins A and E